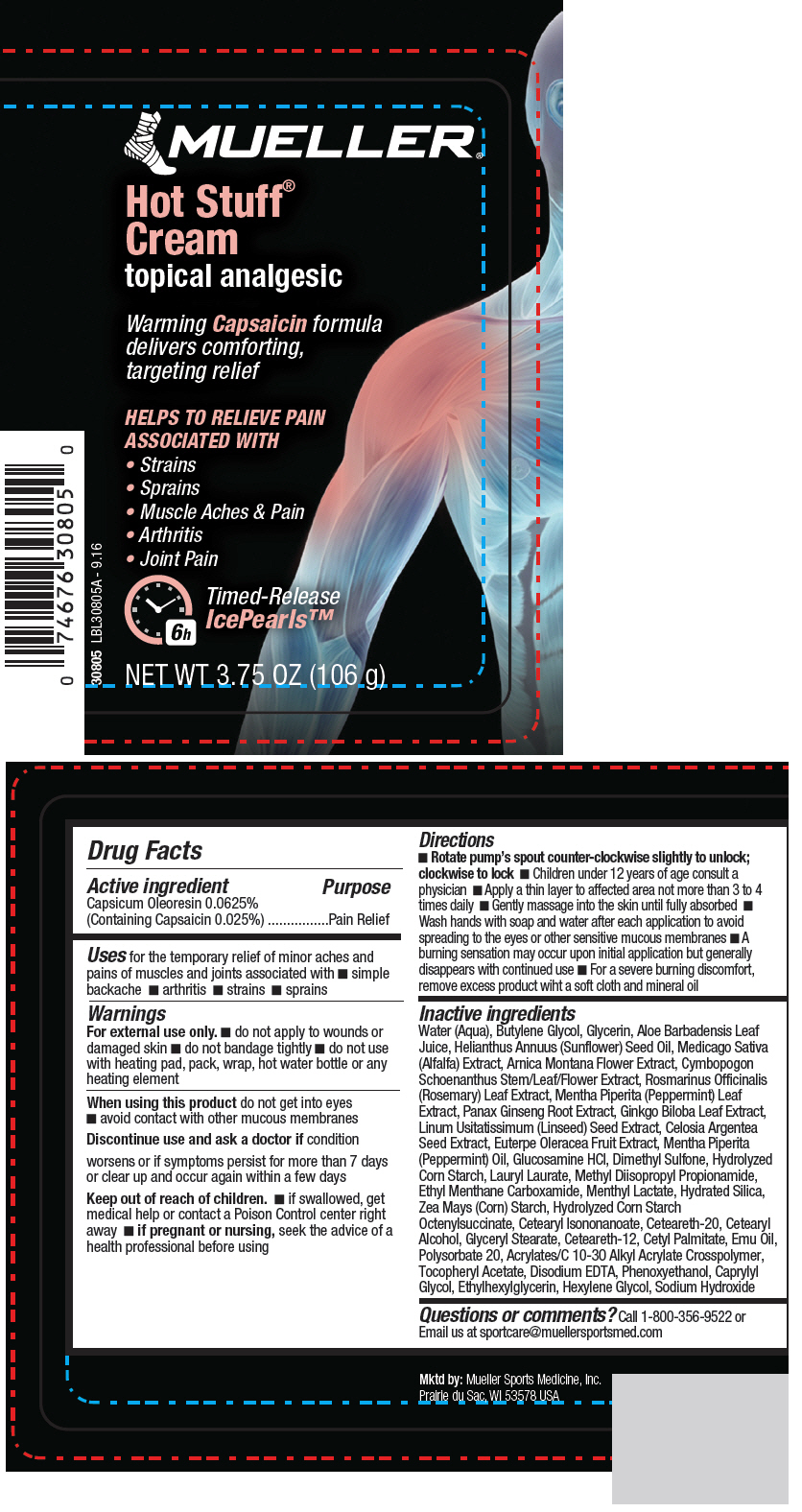 DRUG LABEL: Hot Stuff
NDC: 52564-308 | Form: CREAM
Manufacturer: Mueller Sports Medicine LLC
Category: otc | Type: HUMAN OTC DRUG LABEL
Date: 20161111

ACTIVE INGREDIENTS: CAPSICUM OLEORESIN 0.0265 g/106 g
INACTIVE INGREDIENTS: WATER; BUTYLENE GLYCOL; GLYCERIN; ALOE VERA LEAF; SUNFLOWER OIL; ALFALFA; ARNICA MONTANA FLOWER; ROSEMARY; MENTHA PIPERITA LEAF; ASIAN GINSENG; GINKGO; FLAX SEED; ACAI; PEPPERMINT OIL; GLUCOSAMINE HYDROCHLORIDE; DIMETHYL SULFONE; LAURYL LAURATE; METHYL DIISOPROPYL PROPIONAMIDE; ETHYL MENTHANE CARBOXAMIDE; MENTHYL LACTATE, (-)-; HYDRATED SILICA; STARCH, CORN; CETEARYL ISONONANOATE; POLYOXYL 20 CETOSTEARYL ETHER; CETOSTEARYL ALCOHOL; GLYCERYL MONOSTEARATE; CETEARETH-12; CETYL PALMITATE; EMU OIL; POLYSORBATE 20; .ALPHA.-TOCOPHEROL ACETATE; EDETATE DISODIUM ANHYDROUS; PHENOXYETHANOL; CAPRYLYL GLYCOL; ETHYLHEXYLGLYCERIN; HEXYLENE GLYCOL; SODIUM HYDROXIDE

Hot Stuff®

Drug Facts

Active ingredient

Capsicum Oleoresin 0.0625%
(Containing Capsaicin 0.025%)

Purpose

Pain Relief

Uses

for the temporary relief of minor aches and pains of muscles and joints associated with

- simple backache
- arthritis
- strains
- sprains

Warnings

For external use only.

- do not apply to wounds or damaged skin
- do not bandage tightly
- do not use with heating pad, pack, wrap, hot water bottle or any heating element

When using this product do not get into eyes

- avoid contact with other mucous membranes

Discontinue use and ask a doctor if condition worsens or if symptoms persist for more than 7 days or clear up and occur again within a few days

Keep out of reach of children.

- if swallowed, get medical help or contact a Poison Control center right away

PREGNANCY OR BREAST FEEDING

- if pregnant or nursing, seek the advice of a health professional before using

Directions

- Rotate pump's spout counter-clockwise slightly to unlock; clockwise to lock
- Children under 12 years of age consult a physician
- Apply a thin layer to affected area not more than 3 to 4 times daily
- Gently massage into the skin until fully absorbed
- Wash hands with soap and water after each application to avoid spreading to the eyes or other sensitive mucous membranes
- A burning sensation may occur upon initial application but generally disappears with continued use
- For a severe burning discomfort, remove excess product wiht a soft cloth and mineral oil

Inactive ingredients

Water (Aqua), Butylene Glycol, Glycerin, Aloe Barbadensis Leaf Juice, Helianthus Annuus (Sunflower) Seed Oil, Medicago Sativa (Alfalfa) Extract, Arnica Montana Flower Extract, Cymbopogon Schoenanthus Stem/Leaf/Flower Extract, Rosmarinus Officinalis (Rosemary) Leaf Extract, Mentha Piperita (Peppermint) Leaf Extract, Panax Ginseng Root Extract, Ginkgo Biloba Leaf Extract, Linum Usitatissimum (Linseed) Seed Extract, Celosia Argentea Seed Extract, Euterpe Oleracea Fruit Extract, Mentha Piperita (Peppermint) Oil, Glucosamine HCl, Dimethyl Sulfone, Hydrolyzed Corn Starch, Lauryl Laurate, Methyl Diisopropyl Propionamide, Ethyl Menthane Carboxamide, Menthyl Lactate, Hydrated Silica, Zea Mays (Corn) Starch, Hydrolyzed Corn Starch Octenylsuccinate, Cetearyl Isononanoate, Ceteareth-20, Cetearyl Alcohol, Glyceryl Stearate, Ceteareth-12, Cetyl Palmitate, Emu Oil, Polysorbate 20, Acrylates/C 10-30 Alkyl Acrylate Crosspolymer, Tocopheryl Acetate, Disodium EDTA, Phenoxyethanol, Caprylyl Glycol, Ethylhexylglycerin, Hexylene Glycol, Sodium Hydroxide

Questions or comments?

Call 1-800-356-9522 or Email us at sportcare@muellersportsmed.com

PRINCIPAL DISPLAY PANEL - 106 g Bottle Label

MUELLER®

Hot Stuff®
Cream
topical analgesic

Warming Capsaicin formula
delivers comforting,
targeting relief

HELPS TO RELIEVE PAIN
ASSOCIATED WITH

- Strains
- Sprains
- Muscle Aches & Pain
- Arthritis
- Joint Pain

6h
Timed-Release
IcePearls™

30805 LBL30805A - 9.16

NET WT 3.75 OZ (106 g)